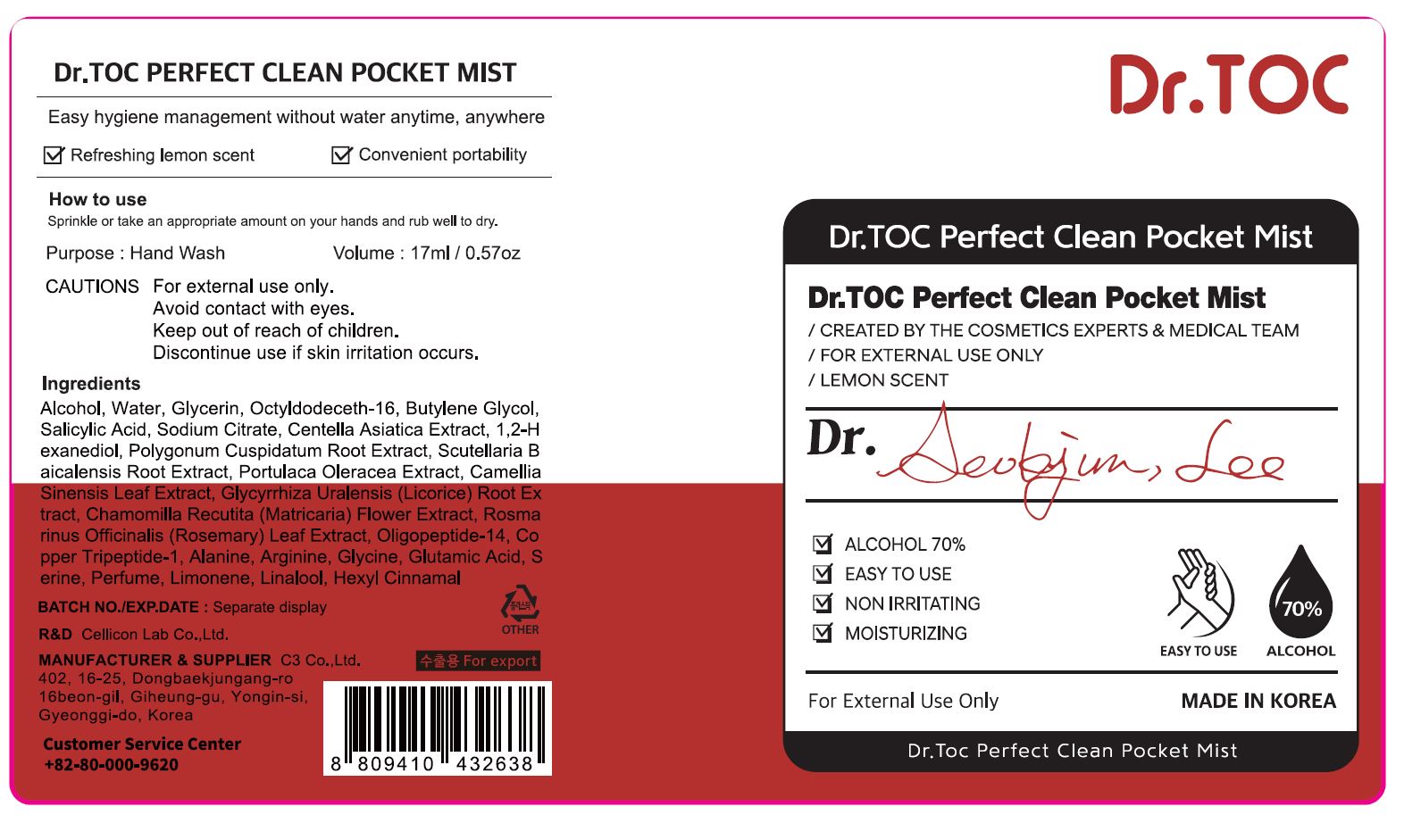 DRUG LABEL: Dr Toc Perfect Clean Pocket Mist
NDC: 70818-029 | Form: SPRAY
Manufacturer: C3 Co., Ltd.
Category: otc | Type: HUMAN OTC DRUG LABEL
Date: 20210214

ACTIVE INGREDIENTS: ALCOHOL 74 mL/100 mL
INACTIVE INGREDIENTS: WATER

C3 Co., Ltd. - isLeaf Hand Cleaning Gel

ACTIVE INGREDIENT

Alcohol

INACTIVE INGREDIENT

Water
Glycerin
Octyldodeceth-16
Fragrance
Limonene
Butylene Glycol
Salicylic Acid
Linalool
Sodium Citrate
Hexyl Cinnamal
Centella Asiatica Extract
1,2-Hexanediol
Polygonum Cuspidatum Root Extract
Scutellaria Baicalensis Root Extract
Portulaca Oleracea Extract
Camellia Sinensis Leaf Extract
Glycyrrhiza Glabra (Licorice) Root Extract
Chamomilla Recutita (Matricaria) Flower Extract
Rosmarinus Officinalis (Rosemary) Leaf Extract
Coppertripeptide-1
Oligopeptide-14
Alanine
Arginine
Glycine
Glutamic Acid
Serine

PURPOSE

Antiseptic

keep out of reach of the children

INDICATIONS AND USAGE

take an appropriate amount on your hands and rub well do dry

WARNINGS

For external use only.

Avoid contact with eyes.

Keep out of reach of children.

Discontinue use if skin irritation occurs.

DOSAGE AND ADMINISTRATION

for external use only